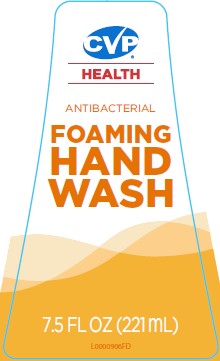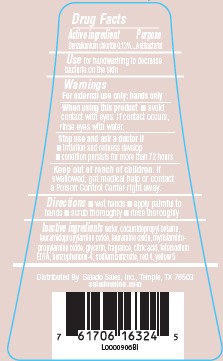 DRUG LABEL: Hand Wash
NDC: 57243-001 | Form: LIQUID
Manufacturer: Salado Sales Inc.
Category: otc | Type: HUMAN OTC DRUG LABEL
Date: 20260206

ACTIVE INGREDIENTS: BENZALKONIUM CHLORIDE 1.3 mg/1 mL
INACTIVE INGREDIENTS: SODIUM BENZOATE; WATER; COCAMIDOPROPYL BETAINE; LAURAMIDOPROPYLAMINE OXIDE; LAURAMINE OXIDE; MYRISTAMIDOPROPYLAMINE OXIDE; GLYCERIN; CITRIC ACID MONOHYDRATE; EDETATE SODIUM; SULISOBENZONE; FD&C RED NO. 4; FD&C YELLOW NO. 5

CVP 466.001/466AB
Antibacterial Foaming Hand Wash

Active ingredient

Benzalkonium chloride 0.13%

purpose

Antibacterial

Use

for handwashing to decrease bacteria on the skin

Warnings

For external use only: Hands only

When using this product

- avoid contact with eyes. If contact occurs, rinse eyes thoroughly with water.

Stop use and ask a doctor if

- irritation and redness develop
- condition persists for more than 72 hours

Keep out of reach of children.

If swallowed, get medical help or contact a Poison Control Center right away.

Directions

- wet hands
- apply palmful to hands
- scrub thoroughly
- rinse thoroughly

Inactive ingredients

water, cocamidopropyl betaine, lauramidopropylamine oxide, lauramine oxide, myristamidopropylamine oxide, glycerin, fragrance, citric acid, tetrasodium EDTA, benzophenone-4, sodium benzoate, red 4, yellow 5

Adverse reactions

Distributed By Salado Sales, Inc. Temple, TX 76503

saladosales.com

principal display panel

CVP®

HEALTH

ANTIBACTERIAL

FOAMING

HAND

WASH

7.5 FL OZ (221 mL)